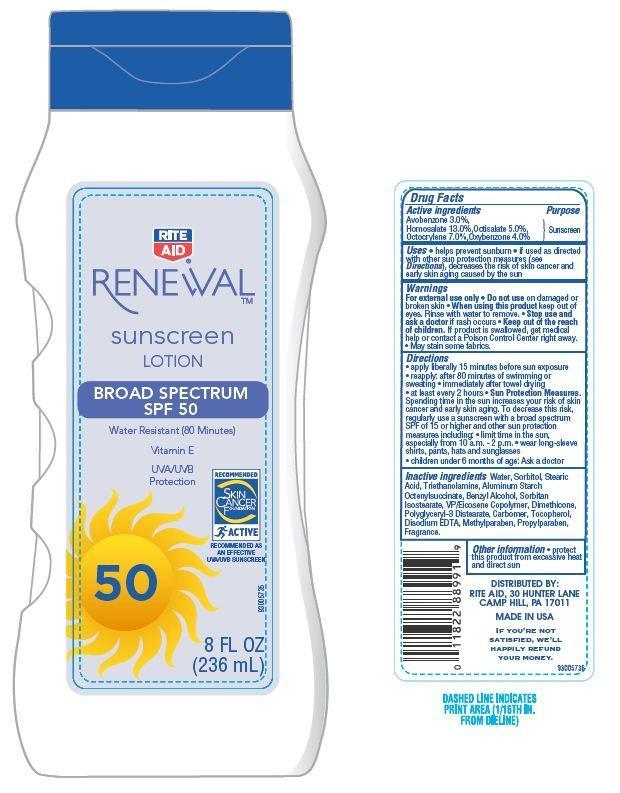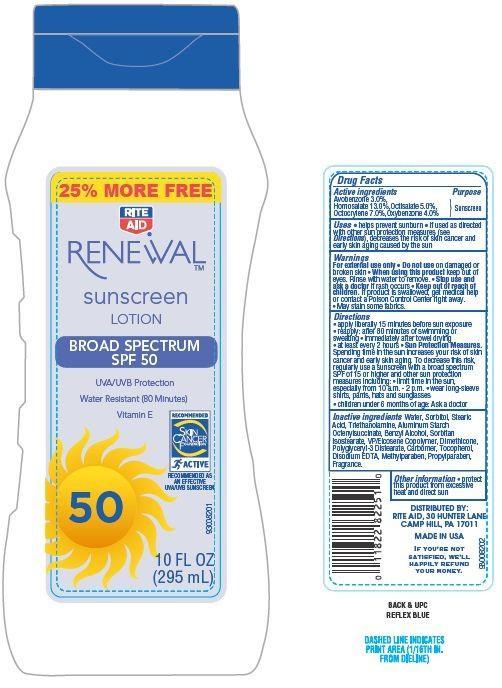 DRUG LABEL: Rite Aid Sunscreen
NDC: 11822-9005 | Form: LOTION
Manufacturer: RITE AID CORPORATION
Category: otc | Type: HUMAN OTC DRUG LABEL
Date: 20130722

ACTIVE INGREDIENTS: AVOBENZONE 3 g/100 g; HOMOSALATE 13 g/100 g; OCTISALATE 5 g/100 g; OCTOCRYLENE 7 g/100 g; OXYBENZONE 4 g/100 g
INACTIVE INGREDIENTS: WATER; SORBITOL; STEARIC ACID; TROLAMINE; ALUMINUM STARCH OCTENYLSUCCINATE; BENZYL ALCOHOL; SORBITAN ISOSTEARATE; DIMETHICONE; POLYGLYCERYL-3 DIISOSTEARATE; METHYLPARABEN; PROPYLPARABEN; TOCOPHEROL; EDETATE DISODIUM

Drug Facts

Active Ingredients

Avobenzone 3.0 %

Homosalate 13.0%

Octisalate 5.0%

Octocrylene 7.0%

Oxybenzone 4.0%

Purpose

Sunscreen

Uses

- helps prevent sunburn
- if used as directed with other sun protection measures (see Directions) decrease the risk of skin cancer and early skin aging caused by sun

Warnings

For External use only

Do not use on damaged or broken skin

When using this product

- keep out of eyes. Rinse with water to remove.

stop use and ask a doctor if

rash occurs.

Keep out of reach of children.

If product is swallowed get medical help or contact a Poison Control Center right away.

- May stain some fabrics.

Other Information

protect this product from excessive heat and direct sun

Directions

- apply literally 15 minutes before sun exposure
- reapply: after 80 minutes of swimming or sweating
- immediately after towel drying
- at least every 2 hours

Sun protection measures.

Spending time in the sun increase your risk of skin cancer and early skin aging. To decrease this risk regularly use a sunscreen with a broad spectrum SPF of 15 or higher and other sun protection measures including:

- Limit time in the sun, especially from 10 am - 2 pm
- Wear long sleeves shirts, pants, hats and sunglasses
- children under 6 month of age: Ask a doctor

Inactive Ingredients

Water, Sorbitol, Stearic Acid, Triethanolamine, Aluminum Starch Octenylsuccinate, Benzyl Alcohol, Sorbitan Isostearate, VP/Eicosene Copolymer, Dimethicone, Polyglyceryl-3 Distearate, Carbomer, Tocopherol, Disodium EDTA, Methylparaben, Propylparaben, Fragrance.

Principal Display Panel

25% MORE FREE

RITE

AID

RENEWAL

SUNSCREEN

LOTION

BROAD SPECTRUM

SPF 50

UVA/UVB Protection

Water Resistant (80 Minutes)

Vitamin E

RECOMMENDED

SKIN

CANCER

FOUNDATION

RECOMMENDED AS

AN EFFECTIVE

UVA/UVB SUNSCREEN

10 FL OZ

(295 mL)

RITE

AID

RENEWAL

SUNSCREEN

LOTION

BROAD SPECTRUM

SPF 50

UVA/UVB Protection

Water Resistant (80 Minutes)

Vitamin E

RECOMMENDED

SKIN

CANCER

FOUNDATION

RECOMMENDED AS

AN EFFECTIVE

UVA/UVB SUNSCREEN

8 FL OZ

(236 mL)